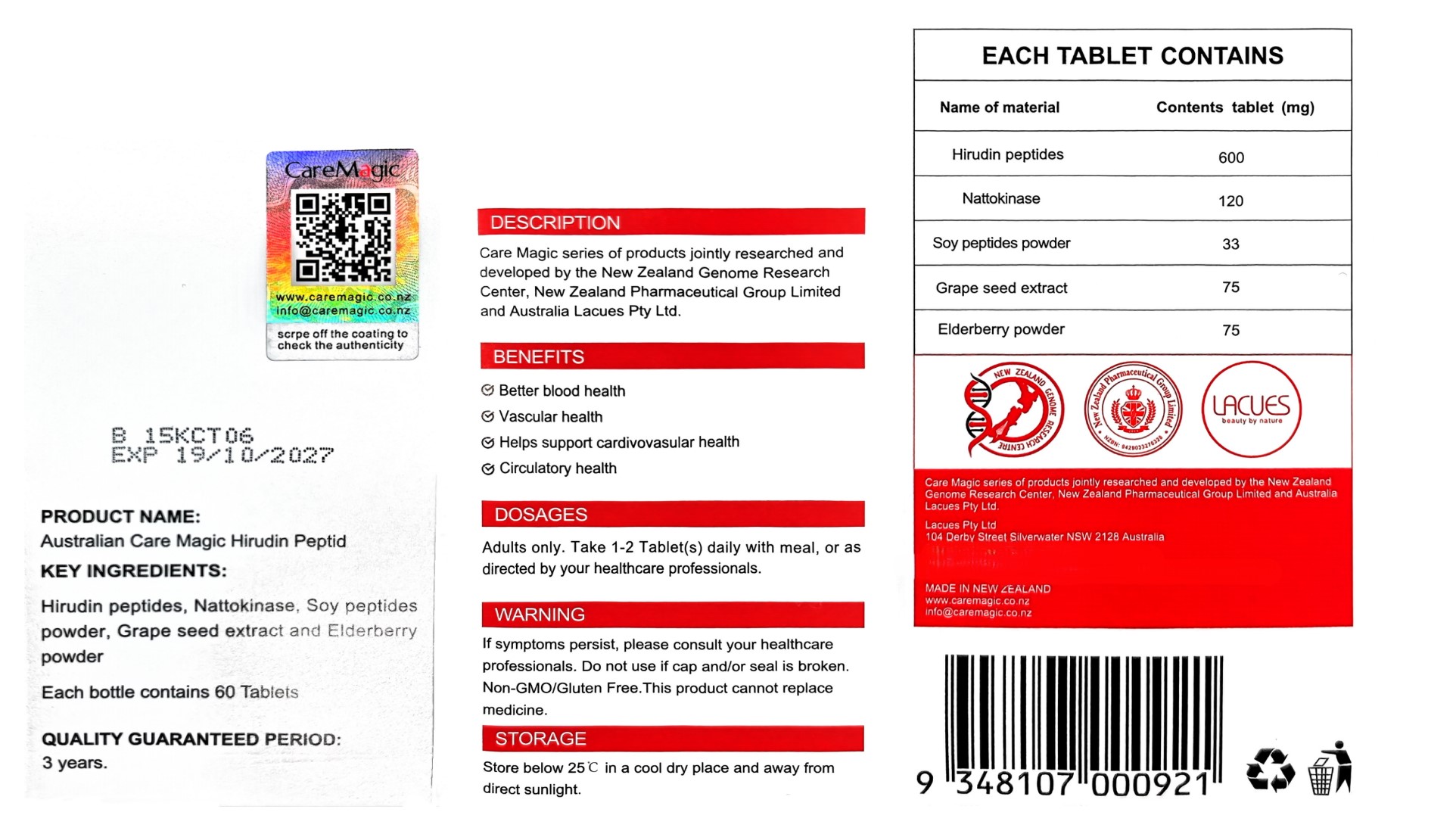 DRUG LABEL: Australian Care Magic Hirudin Peptid
NDC: 85119-001 | Form: PELLET
Manufacturer: LACUES PTY LTD
Category: otc | Type: HUMAN OTC DRUG LABEL
Date: 20250110

ACTIVE INGREDIENTS: HIRUDIN 600 mg/1200 mg
INACTIVE INGREDIENTS: EUROPEAN ELDERBERRY; NATTOKINASE; SOY AMINO ACIDS; GRAPE SEED EXTRACT

ACTIVE INGREDIENT

Hirudin peptides

PURPOSE

Better blood health

Vascular health

Helps support cardivovasular health

Circulatory health

KEEP OUT OF REACH OF CHILDREN

Adults only.

INDICATIONS AND USAGE

Take 1-2 Tablet(s) daily with meal

WARNINGS

lf symptoms persist, please consult your healthcare professionals. Do not use if cap and/or seal is broken .Non-GMO/Gluten Free.This product cannot replace medicine.

DOSAGE AND ADMINISTRATION

Take 1-2 Tablet(s) daily with meal, or asdirected by your healthcare professionals.

INACTIVE INGREDIENT

Nattokinase、 Soy peptidespowder、Grape seed extract and Elderberrypowder、Elderberry powder

WHEN USING

Take 1-2 Tablet(s) daily with meal, or asdirected by your healthcare professionals.